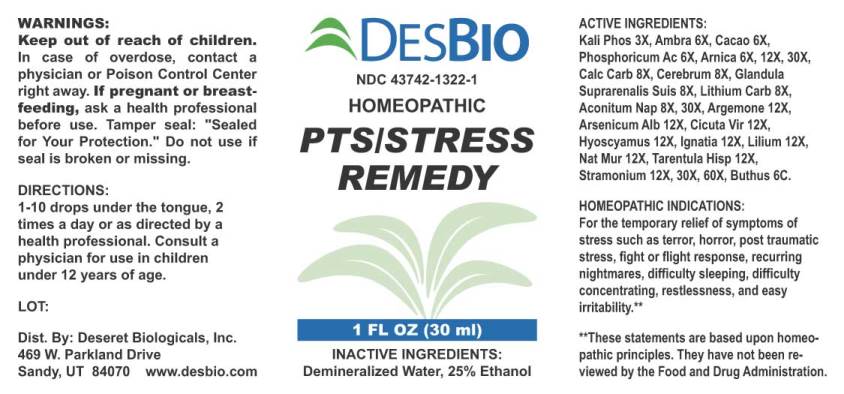 DRUG LABEL: PTS/Stress Remedy
NDC: 43742-1322 | Form: LIQUID
Manufacturer: Deseret Biologicals, Inc.
Category: homeopathic | Type: HUMAN OTC DRUG LABEL
Date: 20240304

ACTIVE INGREDIENTS: DIBASIC POTASSIUM PHOSPHATE 3 [hp_X]/1 mL; AMBERGRIS 6 [hp_X]/1 mL; COCOA 6 [hp_X]/1 mL; PHOSPHORIC ACID 6 [hp_X]/1 mL; ARNICA MONTANA 6 [hp_X]/1 mL; OYSTER SHELL CALCIUM CARBONATE, CRUDE 8 [hp_X]/1 mL; SUS SCROFA CEREBRUM 8 [hp_X]/1 mL; SUS SCROFA ADRENAL GLAND 8 [hp_X]/1 mL; LITHIUM CARBONATE 8 [hp_X]/1 mL; ACONITUM NAPELLUS 8 [hp_X]/1 mL; ARGEMONE MEXICANA 12 [hp_X]/1 mL; ARSENIC TRIOXIDE 12 [hp_X]/1 mL; CICUTA VIROSA ROOT 12 [hp_X]/1 mL; HYOSCYAMUS NIGER 12 [hp_X]/1 mL; STRYCHNOS IGNATII SEED 12 [hp_X]/1 mL; LILIUM LANCIFOLIUM WHOLE FLOWERING 12 [hp_X]/1 mL; SODIUM CHLORIDE 12 [hp_X]/1 mL; LYCOSA TARANTULA 12 [hp_X]/1 mL; DATURA STRAMONIUM 12 [hp_X]/1 mL; ANDROCTONUS AUSTRALIS VENOM 6 [hp_C]/1 mL
INACTIVE INGREDIENTS: WATER; ALCOHOL

Drug Facts:

ACTIVE INGREDIENTS:

Kali Phosphoricum 3X, Ambra Grisea 6X, Cacao 6X, Phosphoricum Acidum 6X, Arnica Montana 6X, 12X, 30X, Calcarea Carbonica 8X, Cerebrum Suis 8X, Glandula Suprarenalis Suis 8X, Lithium Carbonicum 8X, Aconitum Napellus 8X, 30X, Argemone Mexicana 12X, Arsenicum Album 12X, Cicuta Virosa 12X, Hyoscyamus Niger 12X, Ignatia Tigrinum 12X, Natrum Muriaticum 12X, Tarentula Hispanica 12X, Stramonium 12X, 30X, 60X, Buthus Australis 6C.

HOMEOPATHIC INDICATIONS:

For the temporary relief of symptoms of stress such as terror, horror, post traumatic stress, fight or flight response, recurring nightmares, difficulty sleeping, difficulty concentrating, restlessness, and easy irritability.**

**These statements are based upon homeopathic principles. They have not been reviewed by the Food and Drug Administration.

WARNINGS:

If pregnant or breastfeeding, ask a health professional before use.

Keep out of reach of children. In case of overdose, get medical help or contact a Poison Control Center right away.

Do not use if tamper evident seal is broken or missing.

Store in a cool, dry place.

Keep out of reach of children. In case of overdose, get medical help or contact a Poison Control Center right away.

DIRECTIONS:

1-10 drops under the tongue, 2 times a day or as directed by a health professional. Consult a physician for use in children under 12 years of age.

HOMEOPATHIC INDICATIONS:

For the temporary relief of symptoms of stress such as terror, horror, post traumatic stress, fight or flight response, recurring nightmares, difficulty sleeping, difficulty concentrating, restlessness, and easy irritability.**

**These statements are based upon homeopathic principles. They have not been reviewed by the Food and Drug Administration.

INACTIVE INGREDIENTS:

Demineralized Water, 25% Ethanol.

QUESTIONS:

Dist. By: Deseret Biologicals, Inc.

469 W. Parkland Drive

Sandy, UT 84070 www.desbio.com

PACKAGE LABEL DISPLAY:

DESBIO

NDC 43742-1322-1

HOMEOPATHIC

PTS/STRESS

REMEDY

1 FL OZ (30 ml)